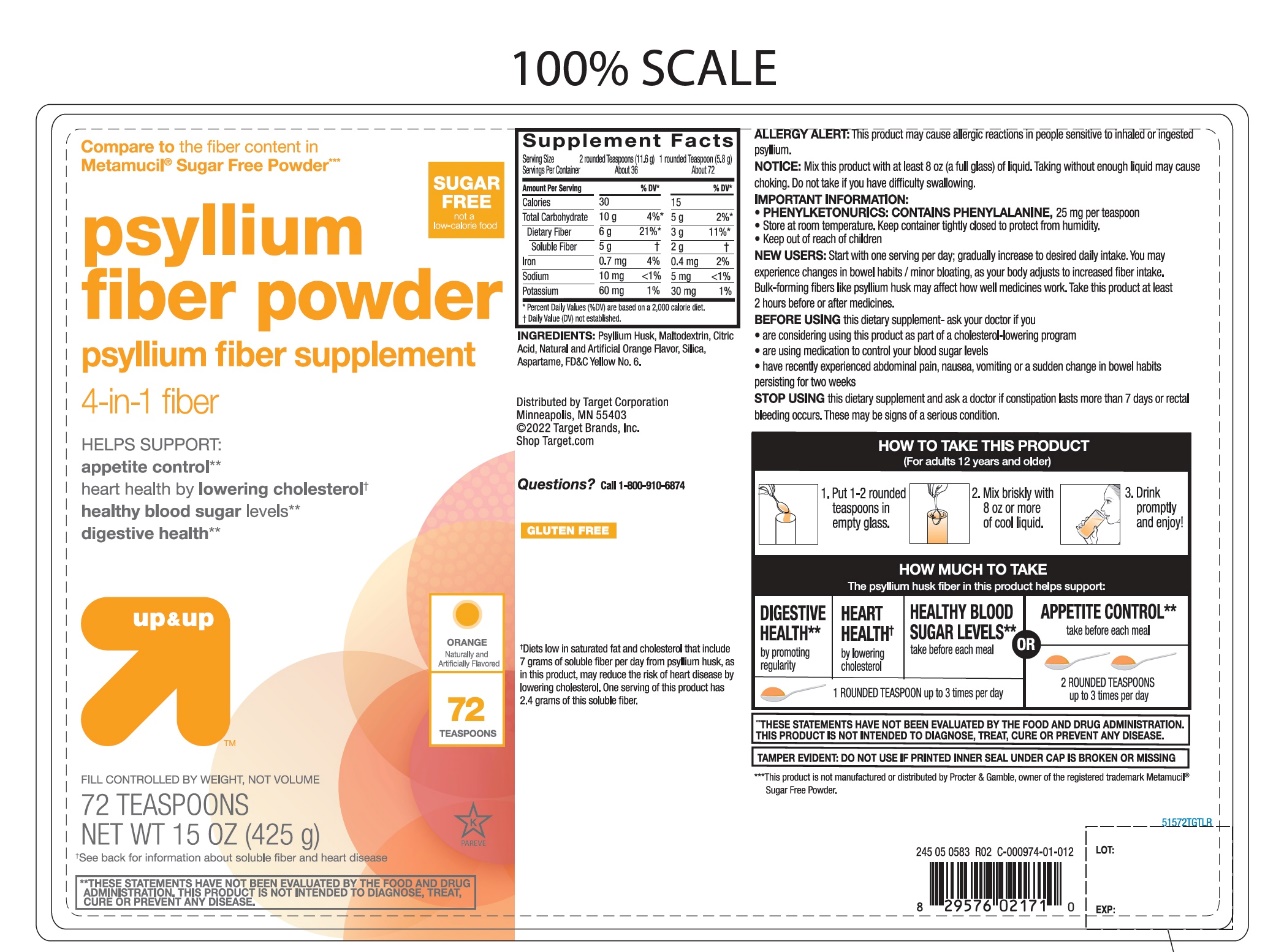 DRUG LABEL: up and up fiber therapy
NDC: 11673-669 | Form: POWDER
Manufacturer: TARGET CORPORATION
Category: otc | Type: HUMAN OTC DRUG LABEL
Date: 20251105

ACTIVE INGREDIENTS: PSYLLIUM HUSK 3.4 g/5.79 g
INACTIVE INGREDIENTS: ASPARTAME; ANHYDROUS CITRIC ACID; FD&C YELLOW NO. 6; MALTODEXTRIN; SILICON DIOXIDE

TARGET Fiber 100% NATURAL PSYLLIUM HUSK Orange Flavor Sugar free 72 Teaspoon Doses

Drug Facts

Active ingredient: (in each teaspoon)

Psyllium husk approximately 3.4 g

Purpose

Bulk-forming Laxative

Uses:

- for relief of occasional constipation (irregularity)
- generally produces bowel movement in 12-72 hours

Warnings:

Choking:

Taking this product without adequate fluid may cause it to swell and block your throat or esophagus and may cause choking. Do not take this product if you have difficulty in swallowing. If you experience chest pain, vomiting, or difficulty in swallowing or breathing after taking this product, seek immediate medical attention.

Allergy alert:

This product may cause allergic reaction in people sensitive to inhaled or ingested psyllium.

Ask a doctor before use if you have

- a sudden change in bowel habits persisting for 2 weeks
- abdominal pain, nausea or vomiting

Stop use and ask a doctor if

- constipation lasts more than 7 days
- rectal bleeding occurs

These may be signs of a serious condition.

Keep out of reach of children.In case of overdose, get medical help or contact a Poison Control Center right away at 1-800-222-1222.

Directions:

Put one dose into an empty glass. Mix this product (child or adult dose) with at least 8 ounces (a full glass) of water or other fluid. Taking this product without enough liquid may cause choking. See choking warning. Stir briskly and drink promptly. If mixture thickens, add more liquid and stir.

Adults & children 12 years & older: | 1 rounded teaspoon in 8 ounces of liquid at the first sign of irregularity. Can be taken up to 3 times daily.
Children 6-11 yrs : | ½ adult dose in 8 ounces of liquid, up to 3 times daily
Children under 6 yrs: | Consult a doctor

Bulk-forming fibers like psyllium husk may affect how well other medicines work. If you are taking a prescription medicine by mouth, take this product at least 2 hours before or 2 hours after the prescribed medicine.

New Users:

Start with 1 serving per day; gradually increased to desired daily intake. You may initially experience changes in bowel habits or minor bloating, as your body adjusts to increased fiber intake.

Other information:

- each teaspoon contains: potassium 35 mg; sodium 5 mg
- PHENYLKETONURICS: CONTAINS PHENYLALANINE,25 mg per teaspoon
- store at room temperature. Keep the container tightly closed to protect from humidity
- contains a 100% natural, therapeutic fiber

Inactive ingredients:

aspartame, citric acid, FD&C yellow 6, maltodextrin, natural and artificial orange flavor, silica.

Questions or comments?

1-800-910-6874

PRINCIPAL DISPLAY PANEL

NDC 11673-669-72

Compare to the Fiber Content in Metamucil®4 in 1 Multihealth Fiber!™*

FIBER Therapy

100% Natural Psyllium Husk

Multi-Benefit Daily Fiber Supplement

- Helps you feel less hungrybetween meals**
- Helps maintain healthy blood sugarlevels as part of your diet **
- Helps lower cholesterolto promote heart health†
- Promotes digestive health**
- Gluten free

SUGAR FREE

not a low calorie food

ORANGE SMOOTH

Naturally and Artificially Flavored

72 Teaspoon‡Doses

NET WT 15 OZ (425 g)

fill controlled by weight, not volume

K

PAREVE

‡Serving size varies See DIRECTIONS on back panel for more information

†See back for information about soluble fiber and heart disease.

**THESE STATEMENTS HAVE NOT BEEN EVALUATED BY THE FOOD AND DRUG ADMINISTRATION. THIS PRODUCT IS NOT INTENDED TO DIAGNOSE, TREAT, CURE OR PREVENT ANY DISEASE.

DO NOT USE IF PRINTED INNER SEAL IS BROKEN OR MISSING

*This product is not manufactured or distributed by Procter & Gamble, the distributor of Metamucil®4 in 1 MultiHealth Fiber!™.

GLUTEN FREE if you have specific dietary needs, you should consult your doctor before consuming this product.

This product has a low glycemic index, a measure of the effect of dietary carbohydrates on blood sugar levels.

DISTRIBUTED BY:

Target Corporation.

Minneapolis., MN 55403

TM & ©2019